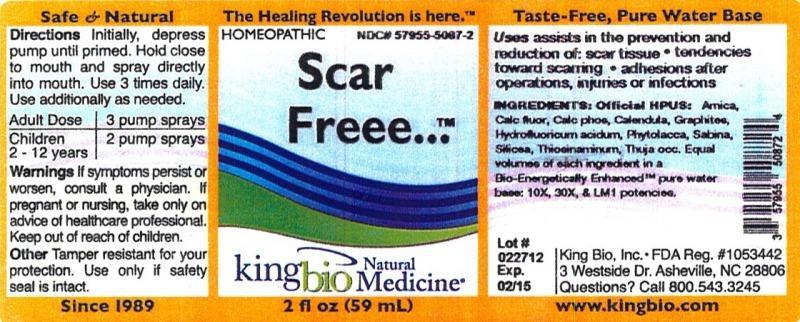 DRUG LABEL: Scar Freee
NDC: 57955-5087 | Form: LIQUID
Manufacturer: King Bio Inc.
Category: homeopathic | Type: HUMAN OTC DRUG LABEL
Date: 20121011

ACTIVE INGREDIENTS: ARNICA MONTANA 10 [hp_X]/59 mL; CALCIUM FLUORIDE 10 [hp_X]/59 mL; TRIBASIC CALCIUM PHOSPHATE 10 [hp_X]/59 mL; CALENDULA OFFICINALIS FLOWERING TOP 10 [hp_X]/59 mL; GRAPHITE 10 [hp_X]/59 mL; HYDROFLUORIC ACID 10 [hp_X]/59 mL; PHYTOLACCA AMERICANA ROOT 10 [hp_X]/59 mL; JUNIPERUS SABINA LEAFY TWIG 10 [hp_X]/59 mL; ALLYLTHIOUREA 10 [hp_X]/59 mL; THUJA OCCIDENTALIS LEAFY TWIG 10 [hp_X]/59 mL
INACTIVE INGREDIENTS: WATER

Scar Freee

Active Ingredients

Official HPUS: Arnica montana, Calcarea fluorica, Calcarea phosphorica, Calendula officinalis, Graphites, Hydrofluoricum acidum, Phytolacca decandra, Sabina, Silicea, Thiosinaminum and Thuja occidentalis.

Inactive Ingredient

Equal volumes of each ingredient in a Bio-Energetically Enhanced pure water base: 10X, 30X and LM1 potencies.

Purpose

Uses assists in the prevention and reduction of:

- scar tissue
- tendencies toward scarring
- adhesions after operations, injuries or infections

Dosage and administration

Directions: Initially, depress pump until primed. Hold close to mouth and spray directly into mouth. Use 3 times daily. Use additionally as needed.

Adult Dose 3 pump sprays

Children 2-12 years 2 pump sprays

Warnings

If symptoms persist or worsen, consult a physician. If pregnant or nursing, take only on advice of healthcare professional. Keep out of reach of children.

Other Tamper resistant for your protection. Use only if safety seal is intact.

Keep out of reach of children.

Purpose

Uses assists in the prevention and reduction of: scar tissue, tendencies toward scarring, adhesions after operations, injuries or infections.

PACKAGE LABEL

King Bio Inc.

3 Westside Drive

Asheville, NC 28806

Question? Call 800.543.3245

www.kingbio.com